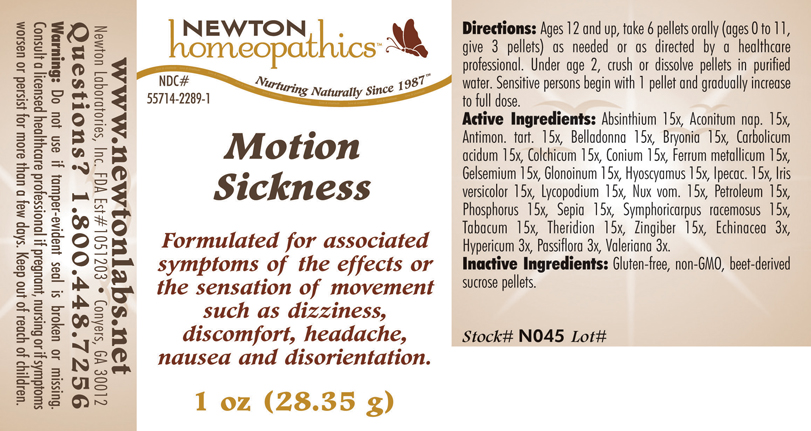 DRUG LABEL: Motion Sickness 
NDC: 55714-2289 | Form: PELLET
Manufacturer: Newton Laboratories, Inc.
Category: homeopathic | Type: HUMAN OTC DRUG LABEL
Date: 20110301

ACTIVE INGREDIENTS: Wormwood 15 [hp_X]/1 g; Aconitum Napellus 15 [hp_X]/1 g; Antimony Potassium Tartrate 15 [hp_X]/1 g; Atropa Belladonna 15 [hp_X]/1 g; Bryonia Alba Root 15 [hp_X]/1 g; Phenol 15 [hp_X]/1 g; Colchicum Autumnale Bulb 15 [hp_X]/1 g; Conium Maculatum Flowering Top 15 [hp_X]/1 g; Iron 15 [hp_X]/1 g; Gelsemium Sempervirens Root 15 [hp_X]/1 g; Nitroglycerin 15 [hp_X]/1 g; Hyoscyamus Niger 15 [hp_X]/1 g; Ipecac 15 [hp_X]/1 g; Iris Versicolor Root 15 [hp_X]/1 g; Lycopodium Clavatum Spore 15 [hp_X]/1 g; Strychnos Nux-vomica Seed 15 [hp_X]/1 g; Kerosene 15 [hp_X]/1 g; Phosphorus 15 [hp_X]/1 g; Sepia Officinalis Juice 15 [hp_X]/1 g; Symphoricarpos Albus Fruit 15 [hp_X]/1 g; Tobacco Leaf 15 [hp_X]/1 g; Theridion Curassavicum 15 [hp_X]/1 g; Ginger 15 [hp_X]/1 g; Echinacea, Unspecified 3 [hp_X]/1 g; Hypericum Perforatum 3 [hp_X]/1 g; Passiflora Incarnata Flowering Top 3 [hp_X]/1 g; Valerian 3 [hp_X]/1 g
INACTIVE INGREDIENTS: Sucrose

Motion Sickness

INDICATIONS & USAGE SECTION

Motion Sickness Formulated for associated symptoms of the effects or the sensation of movement such as dizziness, discomfort, headache, nausea and disorientation.

DOSAGE & ADMINISTRATION SECTION

Directions: Ages 12 and up, take 6 pellets orally (ages 0 to 11, give 3 pellets) as needed or as directed by a healthcare professional. Under age 2, crush or dissolve pellets in purified water. Sensitive persons begin with 1 pellet and gradually increase to full dose.

OTC - ACTIVE INGREDIENT SECTION

Absinthium 15x, Aconitum nap. 15x, Antimon. tart. 15x, Belladonna 15x, Bryonia 15x, Carbolicum acidum 15x, Colchicum 15x, Conium 15x, Ferrum metallicum 15x, Gelsemium 15x, Glonoinum 15x, Hyoscyamus 15x, Ipecac. 15x, Iris versicolor 15x, Lycopodium 15x, Nux vom. 15x, Petroleum 15x, Phosphorus 15x, Sepia 15x, Symphoricarpus racemosus 15x, Tabacum 15x, Theridion 15x, Zingiber 15x, Echinacea 3x, Hypericum 3x, Passiflora 3x, Valeriana 3x.

OTC - PURPOSE SECTION

Formulated for associated symptoms of the effects or the sensation of movement such as dizziness, discomfort, headache, nausea and disorientation.

INACTIVE INGREDIENT SECTION

Inactive Ingredients: Gluten-free, non-GMO, beet-derived sucrose pellets.

QUESTIONS SECTION

www.newtonlabs.net Newton Laboratories, Inc. FDA Est # 1051203 - Conyers, GA 30012
Questions? 1.800.448.7256

WARNINGS SECTION

Warning: Do not use if tamper - evident seal is broken or missing. Consult a licensed healthcare professional if pregnant, nursing or if symptoms worsen or persist for more than a few days. Keep out of reach of children.

OTC - PREGNANCY OR BREAST FEEDING SECTION

Consult a licensed healthcare professional if pregnant, nursing or if symptoms worsen or persist for more than a few days.

OTC - KEEP OUT OF REACH OF CHILDREN SECTION

Keep out of reach of children.